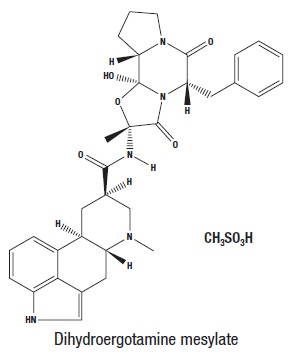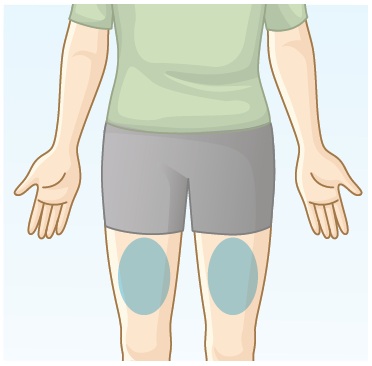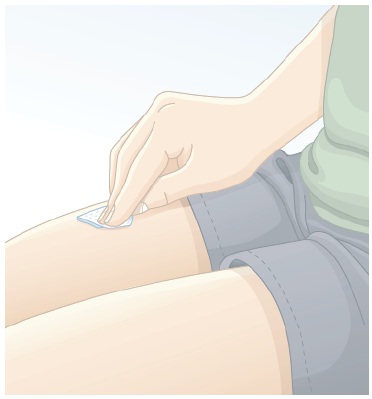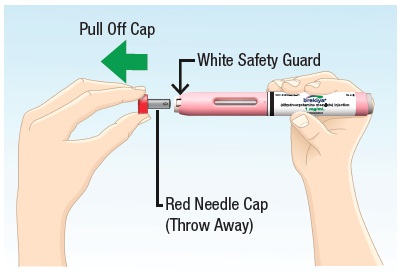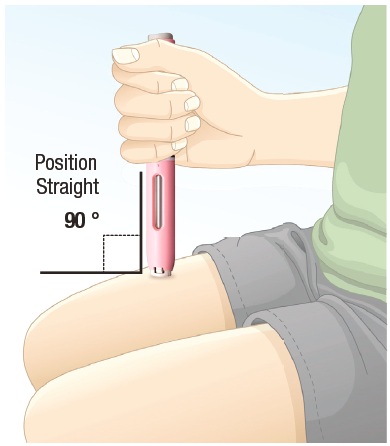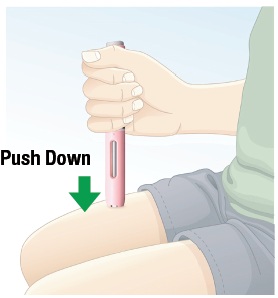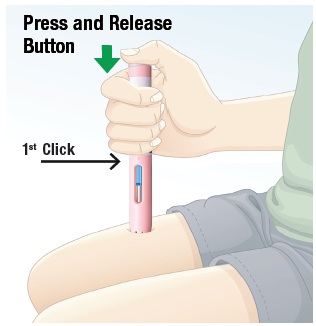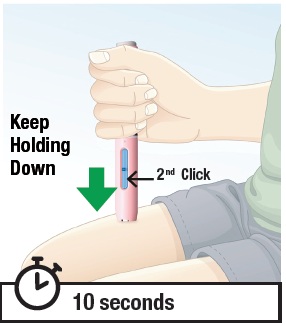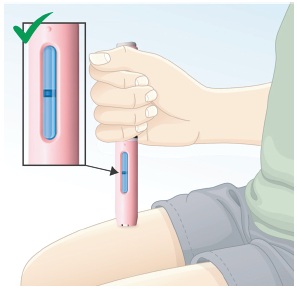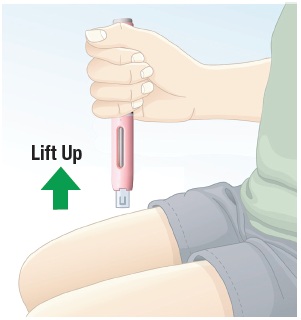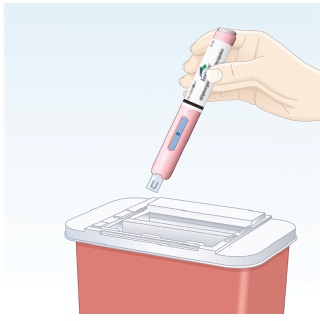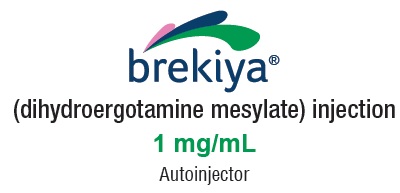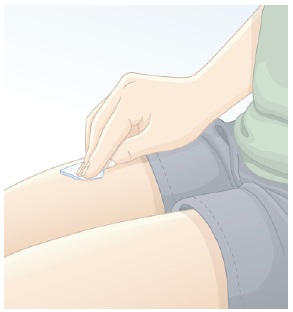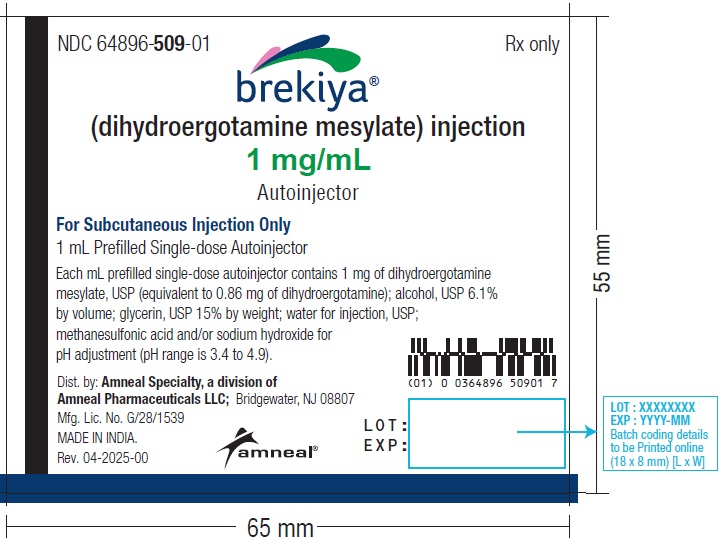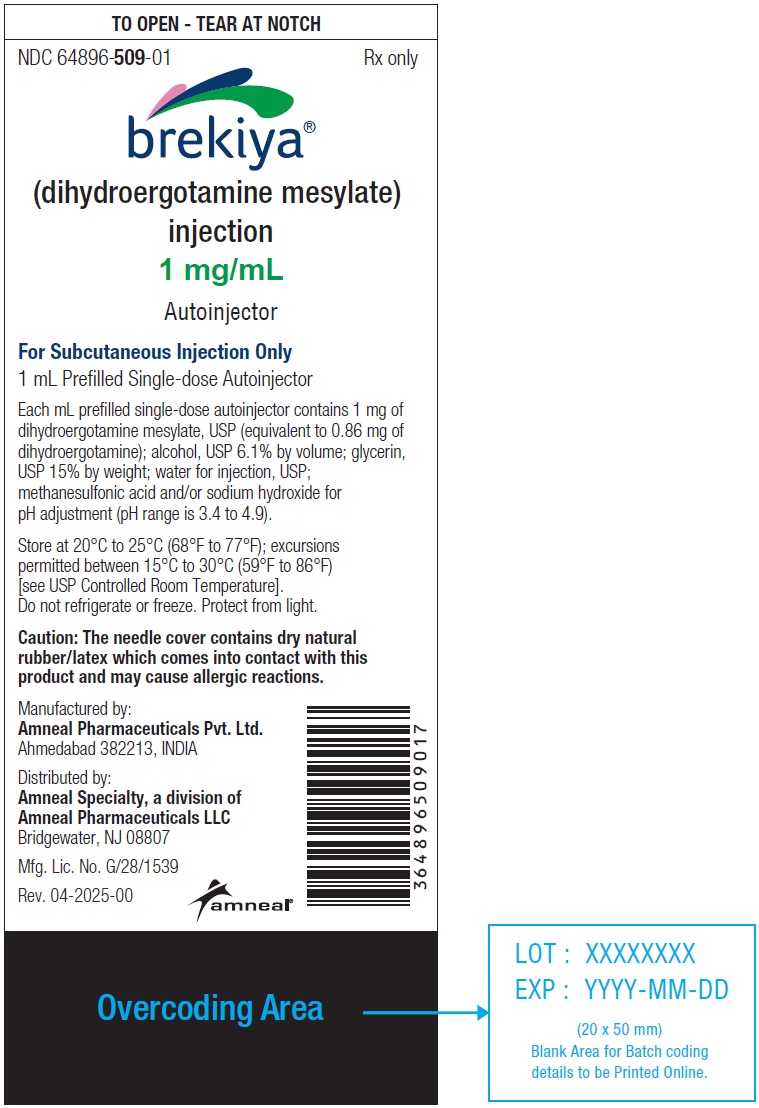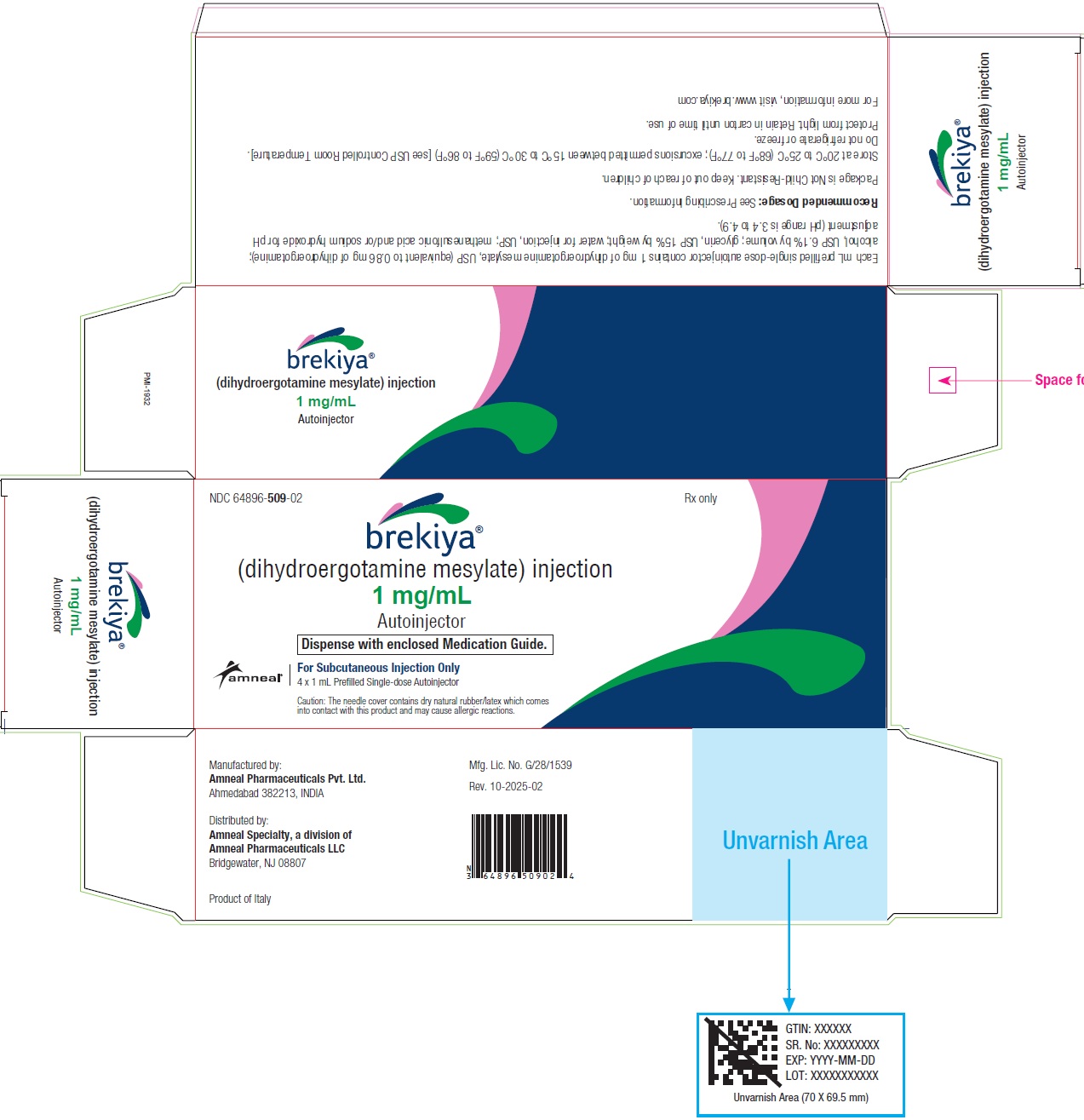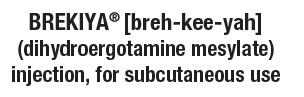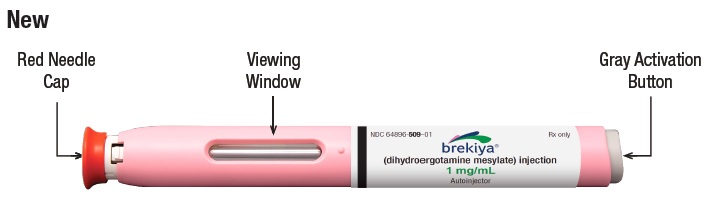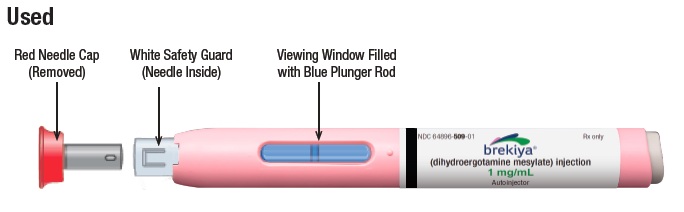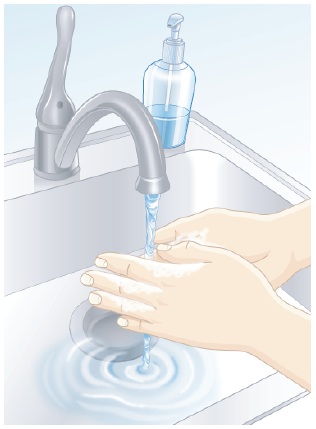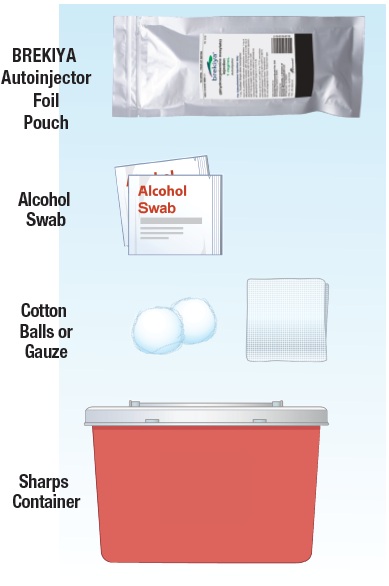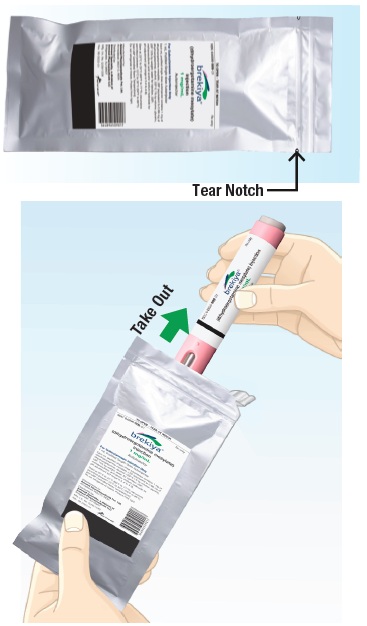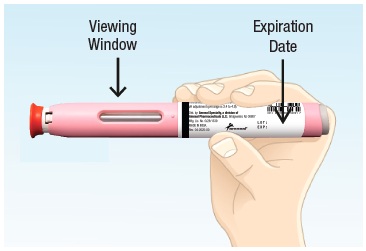 DRUG LABEL: BREKIYA
NDC: 64896-509 | Form: INJECTION
Manufacturer: Amneal Pharmaceuticals LLC
Category: prescription | Type: HUMAN PRESCRIPTION DRUG LABEL
Date: 20251004

ACTIVE INGREDIENTS: DIHYDROERGOTAMINE MESYLATE 1 mg/1 mL
INACTIVE INGREDIENTS: ALCOHOL; GLYCERIN; WATER; METHANESULFONIC ACID; SODIUM HYDROXIDE

HIGHLIGHTS OF PRESCRIBING INFORMATION

These highlights do not include all the information needed to use BREKIYA® safely and effectively. See full prescribing information for BREKIYA®.
BREKIYA® (dihydroergotamine mesylate) injection, for subcutaneous use
Initial U.S. Approval: 1946

WARNING: PERIPHERAL ISCHEMIA FOLLOWING COADMINISTRATION WITH STRONG CYP3A4 INHIBITORS

See full prescribing information for complete boxed warning.

Serious and/or life-threatening peripheral ischemia has been associated with the coadministration of dihydroergotamine with strong CYP3A4 inhibitors including protease inhibitors and macrolide antibiotics. Because CYP3A4 inhibition elevates the serum levels of dihydroergotamine, the risk for vasospasm leading to cerebral ischemia and/or ischemia of the extremities is increased. Hence, concomitant use of BREKIYA with strong CYP3A4 inhibitors is contraindicated [see Contraindications (4) and Warnings and Precautions (5.1)].

1 INDICATIONS AND USAGE

BREKIYA is an ergotamine derivative indicated for the acute treatment of migraine with or without aura and the acute treatment of cluster headaches in adults. (1)

Limitations of Use

BREKIYA is not indicated for the preventive treatment of migraine or for the management of hemiplegic migraine or migraine with brainstem aura. (1)

2 DOSAGE AND ADMINISTRATION

- For subcutaneous injection only. (2.1)
- Recommended dosage is 1 mg administered subcutaneously as a single 1 mL autoinjector. (2.1)
- Do not exceed 3 mg (3 doses) in a 24-hour period. (2.1)
- Do not exceed 6 mg (6 doses) in a week. (2.1)
- Prior to initiation, a cardiovascular evaluation is recommended. (2.2)

3 DOSAGE FORMS AND STRENGTHS

Injection: 1 mg/mL dihydroergotamine mesylate as a 1 mL single-dose autoinjector. (3)

4 CONTRAINDICATIONS

- Concomitant use of strong CYP3A4 inhibitors (4)
- Ischemic heart disease or coronary artery vasospasm (4)
- Uncontrolled hypertension, peripheral arterial diseases, sepsis, following vascular surgery, or severe hepatic or renal impairment (4)
- Concomitant use of other 5-HT1 agonists or ergotamine-containing or ergot-type medications within 24 hours (4)
- Hypersensitivity to dihydroergotamine, ergot alkaloids, latex, or any of the ingredients in BREKIYA (4)
- Concomitant use with peripheral and central vasoconstrictors (4)

5 WARNINGS AND PRECAUTIONS

- Myocardial Ischemia and/or Infarction, Other Cardiac Adverse Reactions, and Fatalities: In patients with risk factors predictive of coronary artery disease, consider first dose administration under medical supervision with an electrocardiogram. (5.2)
- Cerebrovascular Adverse Reactions and Fatalities: Cerebrovascular hemorrhage, subarachnoid hemorrhage, and stroke have been reported; discontinue BREKIYA if suspected. (5.3)
- Other Vasospasm Related Adverse Reactions: BREKIYA may cause vasospasm or elevation in blood pressure. Discontinue if signs or symptoms of vasoconstriction develop. (5.4, 5.5)
- Medication Overuse Headache: Detoxification may be necessary. (5.6)
- Preterm Labor: Advise pregnant women of the risk. (5.7, 8.1)
- Fibrotic Complications: Pleural and retroperitoneal fibrosis have been reported following prolonged daily use of dihydroergotamine mesylate. Do not exceed the BREKIYA dosing guidelines or use for chronic daily administration. (5.8)

6 ADVERSE REACTIONS

Serious cardiac events (including fatal) that have been reported with dihydroergotamine mesylate injection use include coronary artery vasospasm, transient myocardial ischemia, myocardial infarction, ventricular tachycardia, ventricular fibrillation. (6)

To report SUSPECTED ADVERSE REACTIONS, contact Amneal Pharmaceuticals LLC at 1-877-835-5472 or FDA at 1-800-FDA-1088 or www.fda.gov/medwatch

7 DRUG INTERACTIONS

- Beta Blockers/Nicotine: May potentiate/provoke vasoconstriction. (7.3, 7.5)
- Selective Serotonin Reuptake Inhibitors: Weakness, hyperreflexia, and incoordination may occur with coadministration. (7.6)

8 USE IN SPECIFIC POPULATIONS

- Pregnancy: Based on animal data, may cause fetal harm. (8.1)
- Lactation: Advise not to use during breastfeeding. (8.2)

FULL PRESCRIBING INFORMATION

WARNING: PERIPHERAL ISCHEMIA FOLLOWING COADMINISTRATION WITH STRONG CYP3A4 INHIBITORS

Serious and/or life-threatening peripheral ischemia has been associated with the coadministration of dihydroergotamine with strong CYP3A4 inhibitors. Because CYP3A4 inhibition elevates the serum levels of dihydroergotamine, the risk for vasospasm leading to cerebral ischemia and/or ischemia of the extremities is increased. Hence, concomitant use of BREKIYA with strong CYP3A4 inhibitors is contraindicated [see Contraindications (4), Warnings and Precautions (5.1), and Drug Interactions (7.1)].

1 INDICATIONS AND USAGE

BREKIYA is indicated for the acute treatment of migraine with or without aura and the acute treatment of cluster headaches in adults.

Limitations of Use

BREKIYA is not indicated for the preventive treatment of migraine.

BREKIYA is not indicated for the management of hemiplegic migraine or migraine with brainstem aura.

2 DOSAGE AND ADMINISTRATION

2.1 Recommended Dosage

BREKIYA autoinjector is for subcutaneous injection only.

The recommended dose of BREKIYA is 1 mg administered subcutaneously via a single 1 mL autoinjector. The dose may be repeated, as needed, at 1-hour intervals to a total maximum of 3 mg (3 doses) in a 24-hour period.

Do not exceed 6 mg (6 doses) total in a week.

2.2 Assessment Prior to First Dose

Prior to initiation of BREKIYA, a cardiovascular evaluation is recommended [see Warnings and Precautions (5.3)]. For patients with risk factors predictive of coronary artery disease who are determined to have a satisfactory cardiovascular evaluation, it is strongly recommended that administration of the first dose of BREKIYA take place in the setting of an equipped healthcare facility.

2.3 Important Administration Instructions

See the “Instructions for Use” for detailed steps for administering the subcutaneous injection using the autoinjector.

Preparation

- BREKIYA is a prefilled, single-dose disposable autoinjector intended to be given subcutaneously into the skin of the middle thigh.
- Rotate injection sites. Choose an injection site at least 2 inches away from the last injection site.
- Do not inject into moles, scars, birthmarks, or areas where the skin is tender, bruised, red, or hard.
- Parenteral drug products should be inspected visually for particulate matter and discoloration prior to administration, whenever solution and container permit. Carefully examine the liquid medication for discoloration, cloudiness, floating flakes or particles. Administer only if clear and colorless.
  Administration
- Remove the red needle cap by pulling it straight off.
- Position the autoinjector straight onto the cleaned injection site with the white safety guard resting on the skin. Push the autoinjector down and press and release the gray activation button to start the injection. A “click” will sound when the injection starts.
- The autoinjector takes approximately 10 seconds to deliver the dose; when the viewing window is fully blocked (completely blue), the full dose has been administered.

3 DOSAGE FORMS AND STRENGTHS

Injection: 1 mg/mL dihydroergotamine mesylate as a clear, colorless solution in a 1 mL single-dose autoinjector.

4 CONTRAINDICATIONS

BREKIYA is contraindicated in patients:

- with concomitant use of strong CYP3A4 inhibitors [see Warnings and Precautions (5.1) and Drug Interactions (7.1)]
- with ischemic heart disease (e.g., angina pectoris, history of myocardial infarction, or documented silent ischemia) or patients who have clinical symptoms or findings consistent with coronary artery vasospasm, including Prinzmetal's variant angina [see Warnings and Precautions (5.4)]
- with uncontrolled hypertension [see Warnings and Precautions (5.5)]
- with peripheral arterial disease
- with sepsis
- following vascular surgery
- with severe hepatic impairment
- with severe renal impairment
- with known hypersensitivity to dihydroergotamine, ergot alkaloids, latex, or any of the ingredients in BREKIYA [see Warnings and Precautions (5.9)]
- with recent use (i.e., within 24 hours) of other 5-HT1 agonists, ergotamine-containing or ergot-type medications [see Drug Interactions (7.2)]
- with concomitant use of peripheral and central vasoconstrictors because the combination may result in additive or synergistic elevation of blood pressure [see Warnings and Precautions (5.5)]

5 WARNINGS AND PRECAUTIONS

5.1 Peripheral Ischemia Following Coadministration with Strong CYP3A4 Inhibitors

Serious and/or life-threatening peripheral ischemia has been associated with the coadministration of dihydroergotamine and strong CYP3A4 inhibitors. Because CYP3A4 inhibition elevates the serum levels of dihydroergotamine, the risk for vasospasm leading to cerebral ischemia and/or and ischemia of the extremities is increased. Hence, concomitant use of BREKIYA with strong CYP3A4 inhibitors is contraindicated [see Contraindications (4) and Drug Interactions (7.1)].

5.2 Myocardial Ischemia and/or Infarction, Other Cardiac Adverse Reactions, and Fatalities

The potential for cardiac adverse reactions exists with BREKIYA treatment. Serious adverse cardiac events, including some that have been fatal, have occurred following use of dihydroergotamine mesylate. These events have included acute myocardial infarction, life-threatening disturbances of cardiac rhythm (e.g., ventricular tachycardia and ventricular fibrillation), coronary artery vasospasm, and transient myocardial ischemia.

Prior to initiation of BREKIYA, a cardiovascular evaluation is recommended to determine if the patient is free of coronary artery and ischemic myocardial disease or other significant underlying cardiovascular disease. If, during the cardiovascular evaluation, the patient’s medical history (including risk factors), or electrocardiographic investigation findings are consistent with coronary artery vasospasm or myocardial ischemia, BREKIYA should not be administered [see Contraindications (4)].

For patients with risk factors predictive of coronary artery disease (e.g., hypertension, hypercholesterolemia, smoker, obesity, diabetes, strong family history of coronary artery disease, females who are surgically or physiologically postmenopausal, or males who are over 40 years of age) who are determined to have a satisfactory cardiovascular evaluation, it is strongly recommended that administration of the first dose of BREKIYA take place in the setting of an equipped healthcare facility, unless the patient has previously received dihydroergotamine. During the interval immediately following the first use of BREKIYA, an electrocardiogram is recommended in those patients with risk factors because ischemia can occur in the absence of clinical symptoms.

5.3 Cerebrovascular Adverse Reactions and Fatalities

The potential for adverse cerebrovascular events exists with BREKIYA treatment. Cerebral hemorrhage, subarachnoid hemorrhage, stroke, and other cerebrovascular events have been reported in patients treated with dihydroergotamine mesylate; and some have resulted in fatalities. In a number of cases, it appears possible that the cerebrovascular events were primary, the dihydroergotamine mesylate having been administered in the incorrect belief that the symptoms experienced were a consequence of migraine, when they were not. It should be noted that patients with migraine may be at increased risk of certain cerebrovascular events (e.g., stroke, hemorrhage, transient ischemic attack). Discontinue BREKIYA if a cerebrovascular event is suspected.

5.4 Other Vasospasm Related Adverse Reactions

BREKIYA, like other ergot alkaloids, may cause vasospastic reactions other than coronary artery vasospasm. Myocardial, peripheral vascular, and colonic ischemia have been reported with dihydroergotamine mesylate.

Dihydroergotamine associated vasospastic phenomena may also cause muscle pains, numbness, coldness, pallor, and cyanosis of the digits. In patients with compromised circulation, persistent vasospasm may result in gangrene or death. BREKIYA should be discontinued immediately if signs or symptoms of vasoconstriction develop.

Patients who experience other symptoms or signs suggestive of decreased arterial flow, such as ischemic bowel syndrome or Raynaud’s syndrome following the use of any 5-HT agonist, including BREKIYA, should be evaluated by a healthcare provider.

5.5 Increase in Blood Pressure

Significant elevation in blood pressure has been reported on rare occasions in patients with and without a history of hypertension treated with dihydroergotamine mesylate. BREKIYA is contraindicated in patients with uncontrolled hypertension [see Contraindications (4)].

An 18% increase in mean pulmonary artery pressure was seen following dosing with another 5-HT1 agonist in a study evaluating subjects undergoing cardiac catheterization.

5.6 Medication Overuse Headache

Overuse of acute migraine drugs (e.g., ergotamines, triptans, opioids, or a combination of these drugs for 10 or more days per month) may lead to exacerbation of headache (i.e., medication overuse headache). Medication overuse headache may present as migraine-like daily headaches or as a marked increase in frequency of migraine attacks. Detoxification of patients including withdrawal of the overused drugs and treatment of withdrawal symptoms (which often includes a transient worsening of headache) may be necessary.

5.7 Preterm Labor

Based on the mechanism of action of dihydroergotamine and findings from the published literature, BREKIYA may cause preterm labor. Avoid use of BREKIYA during pregnancy [see Use in Specific Populations (8.1) and Clinical Pharmacology (12.2)].

5.8 Fibrotic Complications

The potential for fibrotic complications exists with BREKIYA treatment. There have been reports of pleural and retroperitoneal fibrosis in patients following prolonged daily use of dihydroergotamine mesylate. Rarely, prolonged daily use of other ergot alkaloid drugs has been associated with cardiac valvular fibrosis. Rare cases have also been reported in association with the use of dihydroergotamine mesylate; however, in those cases, patients also received drugs known to be associated with cardiac valvular fibrosis.

Administration of BREKIYA should not exceed the dosing guidelines and should not be used for chronic daily administration [see Dosage and Administration (2.1)].

5.9 Hypersensitivity

The rigid needle shield of the BREKIYA autoinjector contains a needle cover (located inside the cap) that contains dry natural rubber, which is made from latex. BREKIYA is contraindicated in patients who have previously shown hypersensitivity to ergot alkaloids or latex.

6 ADVERSE REACTIONS

The following clinically significant adverse reactions are described elsewhere in the labeling:

- Peripheral Ischemia Following Coadministration with Strong CYP3A4 Inhibitors [see Boxed Warning and Warnings and Precautions (5.1)]
- Myocardial Ischemia and/or Infarction, Other Cardiac Adverse Reactions, and Fatalities [see Warnings and Precautions (5.2)]
- Cerebrovascular Adverse Reactions and Fatalities [see Warnings and Precautions (5.3)]
- Other Vasospasm Related Adverse Reactions [see Warnings and Precautions (5.4)]
- Increase in Blood Pressure [see Warnings and Precautions (5.5)]
- Medication Overuse Headache [see Warnings and Precautions (5.6)]
- Preterm Labor [see Warnings and Precautions (5.7)]
- Fibrotic Complications [see Warnings and Precautions (5.8)]
- Hypersensitivity [see Warnings and Precautions (5.9)]

The following adverse reactions associated with the use of dihydroergotamine were identified in clinical studies or postmarketing reports. Because these reactions are reported voluntarily from a population of uncertain size, it is not always possible to reliably estimate their frequency or establish a causal relationship to the drug exposure.

Serious cardiac events, including some that have been fatal, have occurred following use of dihydroergotamine. Events reported have included coronary artery vasospasm, transient myocardial ischemia, myocardial infarction, ventricular tachycardia, and ventricular fibrillation [see Contraindications (4) and Warnings and Precautions (5.2)].

Fibrotic complications have been reported in association with long term use of injectable dihydroergotamine mesylate [see Warnings and Precautions (5.8)].

Vasospasm, paresthesia, hypertension, dizziness, anxiety, dyspnea, headache, flushing, diarrhea, rash, increased sweating, and pleural and retroperitoneal fibrosis occurred after long-term use of dihydroergotamine.

Cases of myocardial infarction and stroke have been reported following the use of dihydroergotamine [see Warnings and Precautions (5.2, 5.3)].

7 DRUG INTERACTIONS

7.1 CYP3A4 Inhibitors

There have been rare reports of serious adverse events in connection with the coadministration of intravenous administration of dihydroergotamine and strong CYP3A4 inhibitors resulting in vasospasm that led to cerebral ischemia and/or ischemia of the extremities [see Warnings and Precautions (5.1)]. The use of strong CYP3A4 inhibitors with BREKIYA is contraindicated [see Contraindications (4)]. Administer moderate CYP3A4 inhibitors with caution.

7.2 Triptans

Triptans (serotonin [5-HT1B/1D receptor agonists) have been reported to cause coronary artery vasospasm, and its effect could be additive with BREKIYA. Therefore, triptans and BREKIYA should not be taken within 24 hours of each other [see Contraindications (4)].

7.3 Beta Blockers

There have been reports that propranolol may potentiate the vasoconstrictive action of ergotamine by blocking the vasodilating property of epinephrine.

7.4 Vasoconstrictors

BREKIYA is contraindicated for use with peripheral and central vasoconstrictors because the combination may cause synergistic elevation of blood pressure [see Warnings and Precautions (5.5)].

7.5 Nicotine

Nicotine may provoke vasoconstriction in some patients, predisposing to a greater ischemic response to ergot therapy [see Warnings and Precautions (5.4)].

7.6 Selective Serotonin Reuptake Inhibitors

Weakness, hyperreflexia, and incoordination have been reported rarely when 5-HT1 agonists have been co-administered with selective serotonin reuptake inhibitors (SSRI’s) (e.g., fluoxetine, fluvoxamine, paroxetine, sertraline).

8 USE IN SPECIFIC POPULATIONS

8.1 Pregnancy

Risk Summary

Available data from published literature indicate an increased risk of preterm delivery with dihydroergotamine, the active moiety in BREKIYA, use during pregnancy. Avoid use of BREKIYA during pregnancy [see Warnings and Precautions (5.7)]. Data collected over decades have shown no increased risk of major birth defects or miscarriage with the use of dihydroergotamine mesylate during pregnancy.

In animal reproduction studies, adverse effects on development were observed following administration of dihydroergotamine mesylate during pregnancy (decreased fetal body weight and/or skeletal ossification) in rats and rabbits or during pregnancy and lactation in rats (decreased body weight and impaired reproductive function in the offspring) at doses that were not associated with maternal toxicity (see Data).

The estimated rate of major birth defects (2.2% to 2.9%) and miscarriage (17%) among deliveries to women with migraine are similar to rates reported in women without migraine. All pregnancies have a background risk of birth defect, loss, or other adverse outcomes. In the U.S. general population, the estimated background risk of major birth defects and miscarriages in clinically recognized pregnancies is 2% to 4% and 15% to 20%, respectively.

Clinical Considerations

Disease-Associated Maternal and/or Embryo/Fetal Risk

Published data have suggested that women with migraine may be at increased risk of preeclampsia and gestational hypertension during pregnancy.

Data

Animal Data

Intranasal administration of dihydroergotamine mesylate to pregnant rats throughout the period of organogenesis resulted in decreased fetal body weight and/or skeletal ossification at doses of 0.16 mg/day or greater. A no-effect level for adverse effects on embryofetal toxicity was not identified in rats. Intranasal administration of dihydroergotamine mesylate to pregnant rabbits throughout organogenesis resulted in decreased skeletal ossification at 3.6 mg/day. The no-effect dose for adverse effects on embryofetal toxicity in rabbits was 1.2 mg/day.

Intranasal administration of dihydroergotamine mesylate to female rats throughout pregnancy and lactation resulted in decreased body weight and impaired reproductive function (decreased mating indices) in the offspring at doses of 0.16 mg/day or greater. A no-effect dose for adverse developmental effects in rats was not established. Effects on offspring development occurred at doses below those that produced evidence of maternal toxicity in these studies.

Dihydroergotamine-induced intrauterine growth retardation has been attributed to reduced uteroplacental blood flow resulting from prolonged vasoconstriction of the uterine vessels and/or increased myometrial tone.

8.2 Lactation

Risk Summary

There are no data on the presence of dihydroergotamine in human milk; however, ergotamine, a related drug, is excreted in human milk. There are reports of vomiting, diarrhea, weak pulse, and unstable blood pressure in breastfed infants exposed to ergotamine. BREKIYA may reduce milk supply because it may decrease prolactin levels.

Because of the potential for reduced milk supply and serious adverse events in the breastfed infant, including diarrhea, vomiting, weak pulse, and unstable blood pressure; advise patients not to breastfeed during treatment with BREKIYA and for 3 days after the last dose. Breast milk supply during this time should be pumped and discarded.

8.4 Pediatric Use

Safety and effectiveness in pediatric patients have not been established.

8.5 Geriatric Use

Clinical studies of dihydroergotamine products did not include sufficient numbers of subjects aged 65 and older to determine whether they respond differently from younger subjects. In general, dose selection for an elderly patient should be cautious, usually starting at the low end of the dosing range, reflecting the greater frequency of decreased hepatic, renal, or cardiac function and of concomitant disease or other drug therapy.

9 DRUG ABUSE AND DEPENDENCE

9.1 Controlled Substance

BREKIYA contains dihydroergotamine (as the mesylate salt), which is not a controlled substance.

9.2 Abuse

Abuse is the intentional, non-therapeutic use of a drug, even once, for its desirable psychological or physiological effects. Currently available data have not demonstrated drug abuse with dihydroergotamine. However, cases of drug abuse in patients on other forms of ergot therapy have been reported.

9.3 Dependence

Physical dependence is a state that develops as a result of physiological adaptation in response to repeated drug use, manifested by withdrawal signs and symptoms after abrupt discontinuation or a significant dose reduction of a drug. Currently available data have not demonstrated physical or psychological dependence with dihydroergotamine. However, cases of psychological dependence in patients on other forms of ergot therapy have been reported.

10 OVERDOSAGE

Symptoms

Excessive doses of dihydroergotamine may result in peripheral signs and symptoms of ergotism.

In general, the symptoms of an acute BREKIYA overdose may be similar to those of an ergotamine overdose, although there may be less pronounced nausea and vomiting with BREKIYA. The symptoms of an ergotamine overdose include the following: numbness, tingling, pain, and cyanosis of the extremities associated with diminished or absent peripheral pulses; respiratory depression; an increase and/or decrease in blood pressure, usually in that order; confusion, delirium, convulsions, and coma; and/or some degree of nausea, vomiting, and abdominal pain.

In laboratory animals, dihydroergotamine was lethal when given at intravenous doses of 44 mg/kg in mice, 130 mg/kg in rats, and 37 mg/kg in rabbits.

Treatment

Treatment includes discontinuance of the drug, local application of warmth to the affected area, the administration of vasodilators, and nursing care to prevent tissue damage. Consider contacting the Poison Help line (1-800-222-1222) or a medical toxicologist for additional overdose management recommendations.

11 DESCRIPTION

BREKIYA (dihydroergotamine mesylate) injection is an ergotamine derivative. Dihydroergotamine mesylate is a white or almost white, crystalline powder. It is slightly soluble in water and chloroform and sparingly soluble in methanol. The chemical name for dihydroergotamine mesylate is ergotaman-3´,6´,18-trione,9,10-dihydro-12´-hydroxy-2´-methyl-5´-(phenylmethyl) monomethanesulfonate (salt). Its molecular weight is 679.8g/mol and its molecular formula is C33H37N5O5∙CH4O3S.

The chemical structure is

BREKIYA is a clear, colorless, sterile solution supplied in 1 mL single-dose autoinjector for subcutaneous administration. Each mL contains 1 mg dihydroergotamine mesylate, USP (equivalent to 0.86 mg of dihydroergotamine). BREKIYA also contains ethanol, USP 6.1% by volume; glycerin, USP 15% by weight; water for injection, USP; may contain methanesulfonic acid and/or sodium hydroxide, NF for pH adjustment. pH range is 3.4 to 4.9.

12 CLINICAL PHARMACOLOGY

12.1 Mechanism of Action

Dihydroergotamine binds with high affinity to 5-HT1Dα and 5-HT1Dβ receptors. The therapeutic activity of dihydroergotamine in migraine is generally attributed to the agonist effects at 5-HT1D receptors.

12.2 Pharmacodynamics

Significant elevation in blood pressure has been reported in patients treated with dihydroergotamine with and without a history of hypertension [see Warnings and Precautions (5.5)].

Dihydroergotamine possesses oxytocic properties.

12.3 Pharmacokinetics

Absorption

Following BREKIYA administration, the mean maximum plasma concentration was 3.8 ng/mL, and the median time from dosing to maximum plasma concentration was approximately 0.4 hours.

Distribution

Dihydroergotamine mesylate is 93% plasma protein bound. The apparent steady-state volume of distribution is approximately 800 liters.

Elimination

Metabolism

Four dihydroergotamine mesylate metabolites have been identified in human plasma following oral administration. The major metabolite, 8´-β-hydroxydihydroergotamine, exhibits affinity equivalent to its parent for adrenergic and 5-HT receptors and demonstrates equivalent potency in several venoconstrictor activity models, in vivo and in vitro. The other metabolites (i.e., dihydrolysergic acid, dihydrolysergic amide, and a metabolite formed by oxidative opening of the proline ring) are of minor importance. Following nasal administration, total metabolites represent only 20% to 30% of plasma AUC. Quantitative pharmacokinetic characterization of the four metabolites has not been performed.

Excretion

The major excretory route of dihydroergotamine is via the bile in the feces. The total body clearance is 1.5 L/min which reflects mainly hepatic clearance. Only 6% to 7% of unchanged dihydroergotamine is excreted in the urine after intramuscular injection. The renal clearance (0.1 L/min) is unaffected by the route of dihydroergotamine administration. The decline of plasma dihydroergotamine after intramuscular or intravenous administration is multi-exponential with a terminal half-life of about 9 hours.

Specific Populations

No studies have been conducted on the effect of renal or hepatic impairment, gender, race, or ethnicity on dihydroergotamine pharmacokinetics [see Contraindications (4)].

Drug Interaction Studies

Pharmacokinetic interactions have been reported in patients treated orally with other ergot alkaloids (e.g., increased levels of ergotamine) and macrolide antibiotics, presumably due to inhibition of cytochrome P450 3A metabolism of the alkaloids. Dihydroergotamine has also been shown to be an inhibitor of cytochrome P450 3A catalyzed reactions and rare reports of ergotism have been obtained from patients treated with dihydroergotamine and macrolide antibiotics (e.g., clarithromycin, erythromycin), and in patients treated with dihydroergotamine and protease inhibitors (e.g., ritonavir), presumably due to inhibition of cytochrome P450 3A metabolism of ergotamine [see Contraindications (4)].

13 NONCLINICAL TOXICOLOGY

13.1 Carcinogenesis, Mutagenesis, Impairment of Fertility

Carcinogenesis

In a 2-year mouse carcinogenicity study, subcutaneous (SC) administration of dihydroergotamine mesylate (0, 0.5, 1.5 or 5 mg/kg/day) resulted in an increased incidence of fibrosarcoma at the injection sites in males and females at the high dose. The higher dose not associated with an increase in tumors (1.5 mg/kg/day) is approximately 2 times the recommended human dose (RHD) of 3 mg/day SC on a body surface area (mg/m^2) basis.

In a 2-year rat carcinogenicity study, intranasal administration of dihydroergotamine mesylate (0, 0.4, 0.8 or 1.6 mg/day for 13 weeks, followed by 0, 0.08, 0.24 or 0.8 mg/day for the remainder of the study) did not result in an increase in tumors.

Mutagenesis

Dihydroergotamine mesylate was negative in an in vitro mutagenicity (Ames) assay and positive in in vitro chromosomal aberration (V79 Chinese hamster cell assay with metabolic activation, and human peripheral blood lymphocyte) assays. Dihydroergotamine was negative in in vivo micronucleus assays in mouse and hamster.

Impairment of Fertility

Intranasal administration of dihydroergotamine to rats at doses up to 1.6 mg/day was not associated with adverse effects on fertility.

16 HOW SUPPLIED/STORAGE AND HANDLING

16.1 How Supplied

BREKIYA (dihydroergotamine mesylate) injection is a clear, colorless, sterile solution of 1 mg/mL dihydroergotamine mesylate available as:

Dosage Unit | Package Size | NDC #
1 mL prefilled single-dose autoinjector | Carton of 4 | NDC 64896-509-02

Caution: The rigid needle shield of the BREKIYA autoinjector contains a needle cover (located inside the cap) that contains dry natural rubber, which is made from latex [see Contraindications (4) and Warnings and Precautions (5.9)].

16.2 Storage and Handling

Store at 20°C to 25°C (68°F to 77°F), excursions permitted to 15°C to 30°C (59°F to 86°F) [see USP controlled room temperature]. Do not refrigerate or freeze. Protect from light. Retain in original pack until time of use.

17 PATIENT COUNSELING INFORMATION

Advise the patient to read the FDA-approved patient labeling (Medication Guide and Instructions for Use).

Serious and/or Life-Threatening Reactions with Coadministration of CYP3A4 Inhibitors

Inform patients that serious and/or life-threatening peripheral ischemia (cerebral ischemia and/or ischemia of the extremities) has been associated with the coadministration of dihydroergotamine and strong CYP3A4 inhibitors, [see Contraindications (4), Warnings and Precautions (5.1), and Drug Interactions (7.1)].

Myocardial Ischemia and/or Infarction, Other Cardiac Events, Cerebrovascular Events, and Fatalities

Inform patients of the risk for serious cardiac, cerebrovascular, and other vasospasm related events. Advise patients to notify their healthcare provider if they develop any risk factors or symptoms while taking BREKIYA. Inform patients that nicotine may provoke vasoconstriction predisposing to a greater ischemic response [see Warnings and Precautions (5.2, 5.3, 5.4, 7.5)].

Increase in Blood Pressure

Inform patients of the risk for significant elevation in blood pressure [see Warnings and Precautions (5.5)].

Medication Overuse Headache

Inform patients that use of drugs to treat migraine attacks for 10 or more days per month may lead to an exacerbation of headache, and encourage patients to record headache frequency and drug use (e.g., by keeping a headache diary) [see Warnings and Precautions (5.6)].

Hypersensitivity

Inform patients that the rigid needle shield of the BREKIYA autoinjector contains a needle cover (located inside the cap) that contains dry natural rubber, which is made from latex, and can cause allergic reactions in latex-sensitive individuals [see Warnings and Precautions (5.9)].

Drug Interactions

Advise patients to inform their healthcare providers if they are taking, or plan to take, any prescription or over-the-counter drugs, since there is a potential for interactions [see Drug Interactions (7)].

Pregnancy

Advise patients of the risk for preterm birth. Advise women to inform their healthcare provider if they are pregnant or intend to become pregnant [see Warnings and Precautions (5.7), Use in Specific Populations (8.1)].

Lactation

Advise patients not to breastfeed during treatment with BREKIYA [see Use in Specific Populations (8.2)].

Important Administration Instructions

Advise patients on the proper use of BREKIYA prior to the initial use and instruct them to read the Instructions for Use [see Dosage and Administration (2.2, 2.3)].

For more information, call 1-877-835-5472.

BREKIYA® is a registered trademark of Amneal Pharmaceuticals LLC.

Distributed by:

Amneal Specialty, a division of Amneal Pharmaceuticals LLC

Bridgewater, NJ 08807

Manufactured by:

Amneal Pharmaceuticals Pvt. Ltd.

Ahmedabad 382213, INDIA

Rev. 10-2025-02

MEDICATION GUIDE

BREKIYA® [breh-kee-yah]

(dihydroergotamine mesylate)

injection, for subcutaneous use

What is the most important information I should know about BREKIYA?

BREKIYA can cause serious side effects, including:

- Serious problems with blood circulation to your legs and feet (peripheral ischemia). BREKIYA can cause peripheral ischemia when you take it with certain medicines known as CYP3A4 inhibitors. Peripheral ischemia may lead to a stroke and death. Stop taking BREKIYA and get emergency medical help right away if you have any of the following symptoms:

- cramping and pain in your legs or hips
- feeling of heaviness or tightness in your leg muscles
- burning or aching pain in your feet or toes while resting
- numbness, tingling, or weakness in your legs
- cold feeling or color changes in 1 or both legs or feet
- slurred speech
- sudden weakness

Do not take medicines known as strong CYP3A4 inhibitors, such as:

- ritonavir

- indinavir

- clarithromycin

- itraconazole

- nelfinavir

- erythromycin

- ketoconazole

These are not all of the medicines that could affect how BREKIYA works. Your healthcare provider can tell you if it is safe to take BREKIYA with other medicines.

What is BREKIYA?

BREKIYA is a prescription medicine used for the acute treatment of migraine with or without aura and acute cluster headaches in adults.

- BREKIYA is not used to prevent migraine.
- BREKIYA is not used to treat other types of headaches such as hemiplegic migraines (that make you unable to move on one side of your body) or basilar migraines (rare form of migraine with aura).

It is not known if BREKIYA is safe and effective in children.

Who should not take BREKIYA? Do not use BREKIYA if you:

- are taking medicines known as strong CYP3A4 inhibitors.
- have heart problems or a history of heart problems.
- have uncontrolled high blood pressure.
- have narrowing of blood vessels in your legs, arms, stomach, or kidneys (peripheral vascular disease).
- have sepsis.
- have had vascular surgery.
- have severe liver problems.
- have severe kidney problems.
- are allergic to dihydroergotamine, ergot alkaloids, latex, or any of the ingredients in BREKIYA. See the end of this Medication Guide for a complete list of ingredients in BREKIYA.
- have taken any of the following medicines in the last 24 hours:

- sumatriptan

- almotriptan

- eletriptan

- frovatriptan

- naratriptan

- rizatriptan

- ergotamine or ergotamine-type medicines

- zolmitriptan

- have taken any medicines that constrict your blood vessels or raise your blood pressure.

Ask your healthcare provider if you are not sure if you are taking any of these medicines. Your healthcare provider can tell you if it is safe to take BREKIYA with other medicines.

Before you take BREKIYA, tell your healthcare provider about all of your medical conditions, including if you:

- have high blood pressure.
- have liver problems.
- have kidney problems.

- have risk factors for heart disease. You have a higher risk for heart disease if you:
  - have high blood pressure
  - have high cholesterol levels
  - smoke
  - are overweight
  - have diabetes
  - have a family history of heart disease
- are taking medicines known as strong CYP3A4 inhibitors.

- are pregnant or plan to become pregnant. BREKIYA may cause preterm labor. BREKIYA should be avoided during pregnancy. Talk to your healthcare provider right away if you are pregnant or want to become pregnant.
- are breastfeeding or plan to breastfeed. BREKIYA may reduce breast milk supply and pass into your breast milk. BREKIYA may be harmful to your baby. Do not breastfeed your baby while taking BREKIYA and for 3 days after you use BREKIYA. Talk with your healthcare provider about the best way to feed your baby if you take BREKIYA.

Tell your healthcare provider about all the medicines you take, including prescription and over-the-counter medicines, vitamins, and herbal supplements. Your healthcare provider will decide if you can take BREKIYA with your other medicines.

Especially tell your healthcare provider if you take:

- sumatriptan

- fluconazole

- propranolol or other medicines that can lower your heart rate

- ergot-type medicine

- grapefruit juice

- any medicines that can increase your blood pressure

- saquinavir

- zileuton

- selective serotonin reuptake inhibitors

- nefazodone

- nicotine

These are not all of the medicines that could affect how BREKIYA works. Your healthcare provider can tell you if it is safe to take BREKIYA with other medicines.

How should I use BREKIYA?

- Certain people should take their first dose of BREKIYA in their healthcare provider’s office or in another medical setting. Ask your healthcare provider if you should take your first dose in a medical setting.
- BREKIYA is for injection under the skin (subcutaneous) only.
- Use BREKIYA exactly as your healthcare provider tells you to use it.
- See the detailed Instructions for Use that comes with BREKIYA for information about how to use BREKIYA.
- Each autoinjector contains 1 dose (1 mg) of BREKIYA.
- If your headache comes back after the first complete dose, you may give yourself up to 2 more doses as needed. Wait at least 1 hour between doses.
- Do not inject more than 3 doses (3 mg) of BREKIYA in a 24-hour period or 6 doses (6 mg) in a 1-week (7 day) period.
- Using BREKIYA for 10 or more days in 1 month may make your headache worse. You should write down when you have headaches and when you take BREKIYA so that you can talk with your healthcare provider about how BREKIYA is working for you.
- If you use too much BREKIYA, call your healthcare provider or the Poison Help line at 1-800-222-1222 or go to the nearest hospital emergency room right away.

What are the possible side effects of BREKIYA?

BREKIYA can cause serious side effects, including:

See “What is the most important information I should know about BREKIYA?”

- Heart attack and other heart problems. Heart problems may lead to death. Stop taking BREKIYA and get emergency medical help right away if you have any of the following symptoms of a heart attack:
  - discomfort in the center of your chest that lasts for more than a few minutes, or that goes away and comes back
  - severe tightness, pain, pressure, or heaviness in your chest, throat, neck, or jaw
  - pain or discomfort in your arms, back, neck, jaw, or stomach
  - shortness of breath with or without chest discomfort
  - breaking out in a cold sweat
  - nausea or vomiting
  - feeling lightheaded
  BREKIYA is not for people with risk factors for heart disease unless a heart exam is done and shows no problem. See “Before you take BREKIYA, tell your healthcare provider about all of your medical conditions, including if you:” for the risk factors for heart disease.
- Stroke. Stop using BREKIYA and get emergency medical help right away if you have any of the following symptoms of a stroke:

- face drooping
- unusual weakness or numbness
- slurred speech

- Changes in color or sensation in your fingers and toes (Raynaud’s syndrome).

- Stomach and intestinal problems (gastrointestinal and colonic ischemic events). Symptoms of gastrointestinal and colonic ischemic events include:

- sudden or severe stomach pain

- constipation or diarrhea

- stomach pain after meals

- bloody diarrhea

- weight loss

- fever

- nausea or vomiting

- Increased blood pressure.
- Medicine overuse headache. Some people who use too much BREKIYA may make their headaches worse (medicine overuse headache). If your headaches get worse, your healthcare provider may decide to stop your treatment with BREKIYA.
- Preterm labor.
- Tissue changes (fibrotic complications). Inflammation and fiber-like tissue that is not normal (fibrosis) can occur around the lungs and stomach.

The most common but serious side effects of BREKIYA are heart problems that happen but may lead to death. These heart problems include:

- temporary squeezing of arteries that supply the heart (coronary artery vasospasm)
- temporary decrease of blood flow to the heart (transient myocardial ischemia)
- heart rhythm problems (ventricular tachycardia and ventricular fibrillation)

Symptoms of these heart problems include:

See “heart attack and other heart problems.”

- numbness or tingling in your fingers and toes.
- muscle pain or cramps in your arms and legs.
- weakness in your legs.
- temporary speeding or slowing of your heart rate.
- swelling or itching.

Tell your healthcare provider if you have any side effect that bothers you or that does not go away. These are not all of the possible side effects of BREKIYA. Call your doctor for medical advice about side effects. You may report side effects to FDA at 1-800-FDA-1088.

How should I store BREKIYA?

- Store BREKIYA at room temperature between 68°F to 77°F (20°C to 25°C).
- Do not refrigerate or freeze BREKIYA.
- Protect BREKIYA from light.
- Keep BREKIYA in the original pack until ready to use.

Keep BREKIYA and all medicines out of the reach of children.

General information about the safe and effective use of BREKIYA.

Medicines are sometimes prescribed for purposes other than those listed in a Medication Guide. Do not use BREKIYA for a condition for which it was not prescribed. Do not give BREKIYA to other people, even if they have the same symptoms you have. It may harm them. You can ask your pharmacist or healthcare provider for information about BREKIYA that is written for health professionals.

What are the ingredients in BREKIYA?

Active ingredient: dihydroergotamine mesylate, USP

Inactive ingredients: ethanol, glycerin, water for injection, methanesulfonic acid or sodium hydroxide.
Distributed by:

Amneal Specialty, a division of Amneal Pharmaceuticals LLC

Bridgewater, NJ 08807
Manufactured by:

Amneal Pharmaceuticals Pvt. Ltd.

Ahmedabad 382213, INDIA
For more information or to report side-effects, call 1-877-835-5472.

Rev. 05-2025-00

This Medication Guide has been approved by the U.S. Food and Drug Administration Issued: 05/2025

INSTRUCTIONS FOR USE

This Instructions for Use contains information on how to inject BREKIYA.

If there are any questions concerning the use of BREKIYA autoinjector, ask your healthcare provider, pharmacist or visit www.brekiya.com.

Important Information You Need to Know Before Injecting BREKIYA

Warnings

- BREKIYA is for injection under the skin (subcutaneous) only.
- The rigid needle shield of the BREKIYA autoinjector contains a needle cover (located inside the cap) that contains dry natural rubber, which is made from latex. Tell your healthcare provider if you are allergic to latex.
- Do not remove the red needle cap until you are ready to inject BREKIYA. Inject BREKIYA right away after removing the red needle cap.
- Do not inject BREKIYA if the autoinjector appears damaged, if the expiration date has passed, if the liquid medicine is cloudy, discolored or has floating flakes or particles.
- Do not throw away (dispose of) the autoinjector into the household trash. Throw away (dispose of) the autoinjector into a FDA-cleared sharps disposal container.

Dosing

- Follow your healthcare provider’s dosing instructions for how often to inject BREKIYA autoinjector.
- Each autoinjector contains 1 dose (1 mg) of BREKIYA. After your first dose of BREKIYA, you may give yourself 2 more doses (for a total of 3 mg) as needed. Wait at least 1 hour between doses.
- Do not inject more than 3 doses (3 mg) of BREKIYA in 1 day (24-hour) period.
- Do not inject more than 6 doses (6 mg) during a 1-week (7-day) period.

Storing BREKIYA Autoinjector

- Store the BREKIYA autoinjector at room temperature between 68°F to 77°F (20°C to 25°C).
- Protect BREKIYA from light.
- Keep BREKIYA in the carton until ready to use.
- Do not refrigerate or freeze BREKIYA.

Keep BREKIYA and all medicines out of the reach of children.

Autoinjector Parts

This autoinjector is a prefilled single dose (1 time use), disposable device that gives a 1 mg subcutaneous (under the skin) injection of BREKIYA. Figure A shows a new and used autoinjector.

Figure A

Preparing to Inject BREKIYA

Step 1: Wash Hands and Gather Supplies

1.1 Before you begin, wash your hands with soap and water (See Figure B).

Figure B

1.2 Gather the following supplies (See Figure C):

- BREKIYA autoinjector foil pouch (inside carton)
- Alcohol swab
- Cotton balls or gauze
- Sharps container [See “Throwing Away (Disposing of) BREKIYA”]

Figure C

Step 2: Remove and Inspect the Autoinjector

2.1 Tear open the foil pouch from the notch to remove the autoinjector (See Figure D).

Figure D

2.2 Check the expiration date printed on the autoinjector (See Figure E). Do not use the autoinjector if the expiration date has passed.

2.3 Check the liquid medicine in BREKIYA by looking through the viewing window (See Figure E). The liquid medicine in BREKIYA should be clear and colorless. It is normal to see one or more air bubbles.

Do not inject if the liquid medicine appears cloudy, discolored, or has floating flakes or particles.

Do not inject if the autoinjector appears to be damaged or broken.

Figure E

Step 3: Select and Prepare Injection Site

3.1 Locate your injection site. BREKIYA autoinjector should be injected into the skin in the middle of your thigh (See Figure F).

Do not inject into moles, scars, birthmarks, or areas where the skin is tender, bruised, red, or hard.

Do not inject through clothing.

Do not inject into the same spot 2 times in a row.

Important: This injection should be at least 2 inches away from the last injection site.

Figure F

3.2 Clean the injection site with an alcohol swab (See Figure G).

Wait for the injection site to air dry before giving the injection. Do not touch the clean injection site again before you inject BREKIYA.

Figure G

Injecting BREKIYA

Step 4: Remove Red Needle Cap and Position the Autoinjector

4.1 Remove the red needle cap by pulling it straight off (See Figure H) and throw it away in the household trash.

Do not bend or twist the cap while removing.

Do not touch the white safety guard after the red needle cap is removed.

Figure H

4.2 Position the autoinjector straight onto the cleaned injection site with the white safety guard resting on the skin (See Figure I).

Figure I

Step 5: Give Injection

5.1 Push the autoinjector down against the skin until you do not see the white safety guard (See Figure J).

Important: Keep downward pressure on the skin throughout the injection process.

Figure J

5.2 Press and release the gray activation button to start the injection (See Figure K). You will hear a “click” sound when the injection starts.

Be Patient. Do not lift the autoinjector after the first click.

Important: If you do not hear a “click” when you press the gray activation button, make sure that the autoinjector is pressed down against the skin, then try again.

Figure K

5.3 Hold the autoinjector down against the skin for at least 10 seconds to make sure you get the full dose of BREKIYA (See Figure L).

Note: You may hear a second “click”, which means you are close to the end of the injection. Whether or not you hear a second “click” you must hold down the autoinjector against your skin for at least 10 seconds.

Do not lift up the autoinjector early.

Figure L

5.4 Make sure the injection is finished by looking at the viewing window. The viewing window will turn completely blue (See Figure M) when the full dose of BREKIYA has been given.

Note: Even if the inspection window is not completely blue, do not try to use the autoinjector again.

Figure M

Throwing Away (Disposing of) BREKIYA Autoinjector

Step 6: Lift and Throw away (dispose of)

6.1 Lift the autoinjector straight up, away from the skin. The white safety guard will drop down and lock over the needle (See Figure N).

Note: If you think that you have not received the full dose, do not repeat the injection using a new autoinjector. Call your healthcare provider right away for assistance.

Figure N

6.2 Throw away (dispose of) the used autoinjector into a FDA-cleared sharps disposal container (See Figure O).

Do not throw away (dispose of) the autoinjector into household trash.

Figure O

6.3 Treat the injection site as needed (See Figure P). It is normal to see a drop of blood or medicine at the injection site. It will not affect your dose.

Figure P

Additional Information on how to Throw Away (Dispose of) BREKIYA

- Put your used needles and syringes in a FDA-cleared sharps disposal container right away after use. Do not throw away (dispose of) loose needles and syringes in your household trash.
- If you do not have an FDA-cleared sharps disposal container, you may use a household container that is:

- made of a heavy-duty plastic,
- can be closed with a tight-fitting, puncture-resistant lid, without sharps being able to come out,
- upright and stable during use,
- leak-resistant, and
- properly labeled to warn of hazardous waste inside the container.

- When your sharps disposal container is almost full, you will need to follow your community guidelines for the right way to dispose of your sharps disposal container. There may be state or local laws about how you should throw away used needles and syringes. For more information about safe sharps disposal, and for specific information about sharps disposal in the state that you live in, go to the FDA’s website at: http://www.fda.gov/safesharpsdisposal
- Do not dispose of your used sharps disposal container in your household trash unless your community guidelines permit this. Do not recycle your used sharps disposal container.

Distributed by:

Amneal Specialty, a division of Amneal Pharmaceuticals LLC

Bridgewater, NJ 08807
Manufactured by:

Amneal Pharmaceuticals Pvt. Ltd.

Ahmedabad 382213, INDIA
For more information or to report side-effects, call 1-877-835-5472.
Rev. 10-2025-01

This Instructions for Use have been approved by the U.S. Food and Drug Administration Issued: 10/2025

PRINCIPAL DISPLAY PANEL

NDC 64896-509-01

BREKIYA® (dihydroergotamine mesylate) injection, 1 mg/mL

Rx only

Autoinjector Label

Amneal Pharmaceuticals LLC

NDC 64896-509-01

BREKIYA® (dihydroergotamine mesylate) injection, 1 mg/mL

Rx only

Pouch

Amneal Pharmaceuticals LLC

NDC 64896-509-02

BREKIYA® (dihydroergotamine mesylate) injection, 1 mg/mL

Rx only

Carton

Amneal Pharmaceuticals LLC